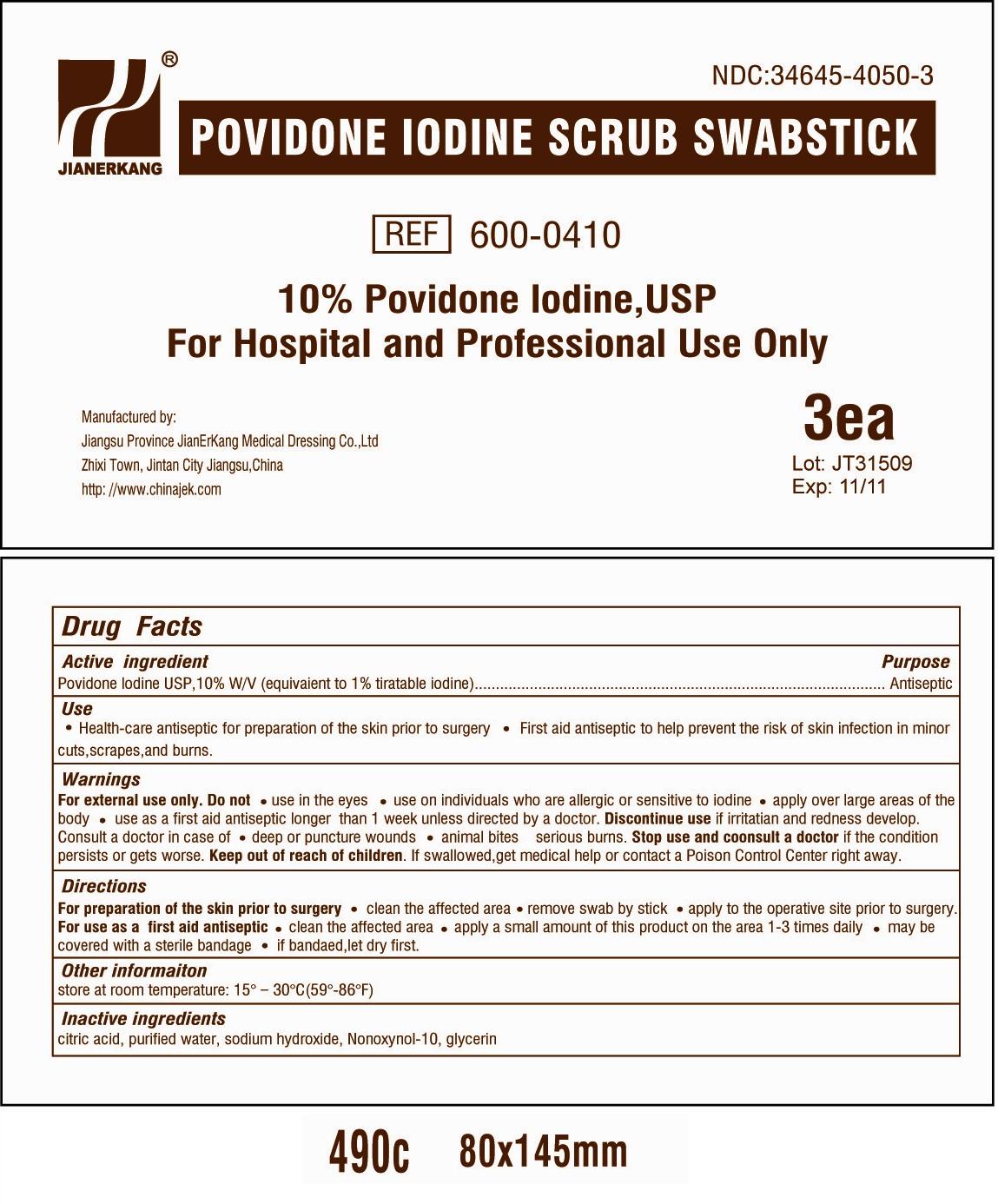 DRUG LABEL: Povidone Iodine Scrub
NDC: 34645-4050 | Form: SWAB
Manufacturer: Jianerkang Medical Co., Ltd
Category: otc | Type: HUMAN OTC DRUG LABEL
Date: 20250123

ACTIVE INGREDIENTS: POVIDONE-IODINE 10 mg/1 mL
INACTIVE INGREDIENTS: WATER; SODIUM HYDROXIDE; NONOXYNOL-10; GLYCERIN; CITRIC ACID MONOHYDRATE

Drug Facts

Active Ingredient

Povidone Iodine USP, 10% W/V (equivalent to 1% titratable iodine)

Purpose

Antiseptic

INDICATIONS AND USAGE

Health-care antiseptic for preparation of the skin prior to surgery First aid antiseptic to help prevent the risk of skin infection in minor cuts, scrapes, and burns Use

Warnings For external use only

DO NOT USE

use in the eyes use on individuals who are allergic or sensitive to iodine apply over larger areas of the body use as a first aid antiseptic longer than 1 week unless by a doctor Do not

DO NOT USE

if irritation and redness develop, consult a doctor in case of deep or puncture wounds animal bites serious burns Discontinue use

Stop use and consult a doctor

if the condition persists or gets worse

KEEP OUT OF REACH OF CHILDREN

If swallowed, get medical help or contact a Poison Control Center right away Keep out of reach of children

Directions

For preparation of the skin prior to surgery

clean the affected area, remove swab by stick apply to the operative site prior to surgery

clean the affected area apply a small amount of this products on the area 1-3 times daily may be covered with a sterile bandage if bandaged, let dry first For use as a first aid antiseptic

Other information

store at room temperature: 15o - 30oC (59o-86oF)

Inactive ingredients

citric acid, purified water, sodium hydroxide, Nonoxynol-10, glycerin

Image of Pouch Label